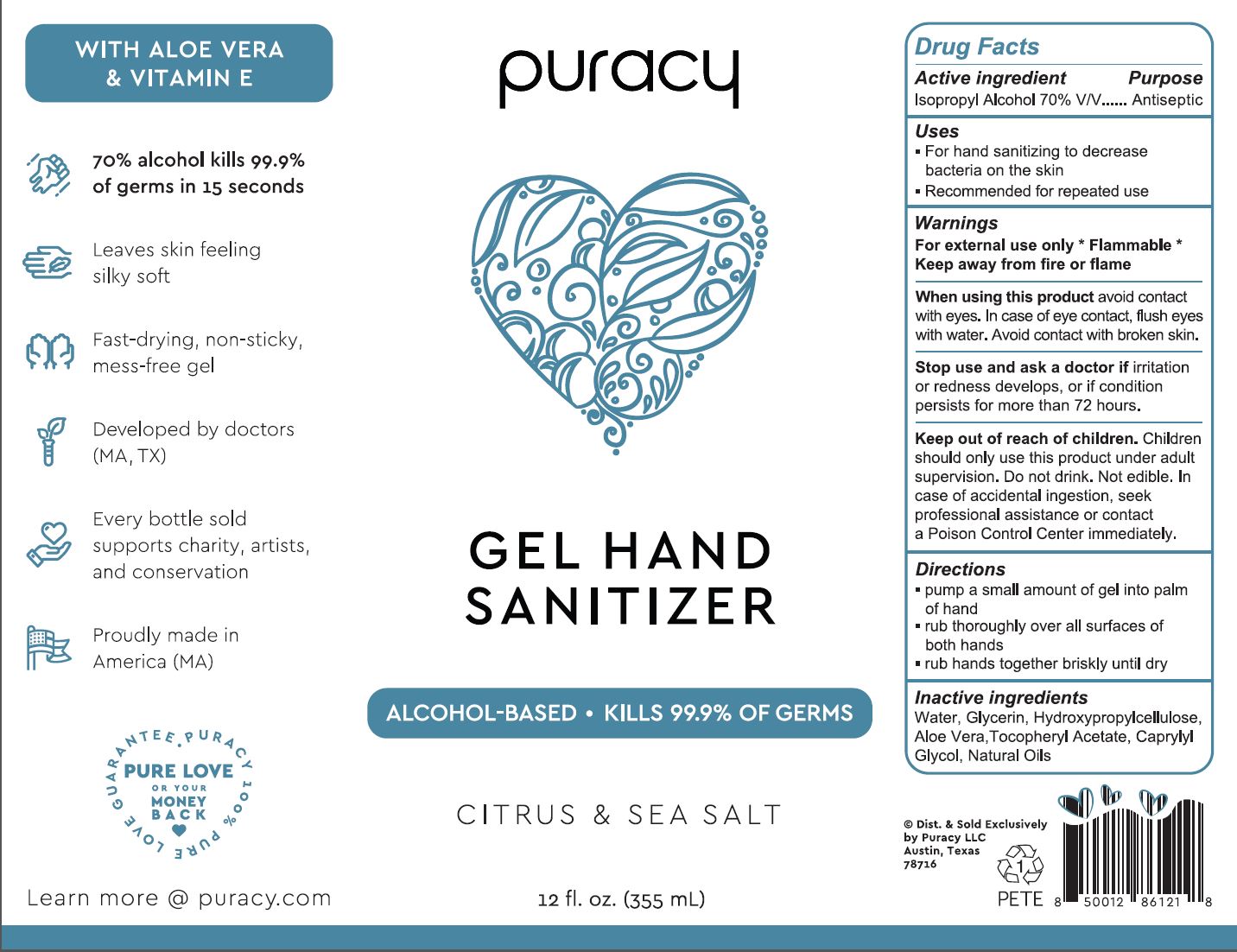 DRUG LABEL: PURACY HAND SANITIZER
NDC: 72905-002 | Form: GEL
Manufacturer: Puracy LLC
Category: otc | Type: HUMAN OTC DRUG LABEL
Date: 20200514

ACTIVE INGREDIENTS: ISOPROPYL ALCOHOL 70 mL/100 mL
INACTIVE INGREDIENTS: .ALPHA.-TOCOPHEROL ACETATE; WATER; GLYCERIN; HYDROXYPROPYL CELLULOSE, UNSPECIFIED; CAPRYLYL GLYCOL; GRAPEFRUIT OIL; ARTEMISIA VULGARIS TOP OIL; GERANIUM OIL, ALGERIAN TYPE; ALOE VERA LEAF

Active ingredient

Isopropyl Alcohol 70% V/V

Purpose

Antiseptic

Uses

- For hand sanitizing to decrease bacteria on the skin
- Recommended for repeated use

Warnings

For external use only *Flammable*

Keep away from fire or flame

When using this product avoid contact with eyes.

In case of eye contact, flush eyes with water.

Avoid contact with broken skin.

Stop use and ask a doctor if irritation or redness develops, or if condition persists for more than 72 hours.

Keep out of reach of children.

Children should only use this product under adult supervision.

Do not drink.

Not edible.

In case of accidental ingestion, seek professional assistance or contact a Poison Control Center immediately.

Directions

- pump a small amount of gel into palm of hand
- rub thoroughly over all surfaces of both hands
- rub hands togerher briskly until dry

Inactive ingredients

Water, Glycerin, Hydroxypropylcellulose, Aloe Vera, Tocopherol Acetate, Caprylyl Glycol, Natural Oils

PACKAGE LABEL

puracy

GEL HAND

SANITIZER

ALCOHOL-BASED KILLS 99.9% OF GERMS

CITRUS and SEA SALT

12 fl. oz. (355 mL)